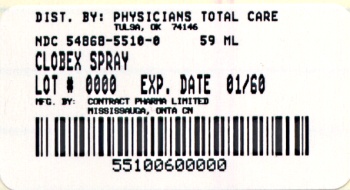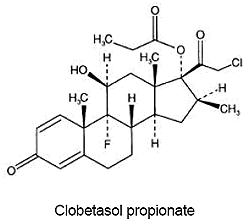 DRUG LABEL: Clobex
NDC: 54868-5510 | Form: SPRAY
Manufacturer: Physicians Total Care, Inc.
Category: prescription | Type: HUMAN PRESCRIPTION DRUG LABEL
Date: 20101228

ACTIVE INGREDIENTS: CLOBETASOL PROPIONATE 0.5  mg/1 mL
INACTIVE INGREDIENTS: ISOPROPYL MYRISTATE; ALCOHOL; UNDECYLENIC ACID; SODIUM LAURYL SULFATE

DESCRIPTION

CLOBEX® (clobetasol propionate) Spray, 0.05% contains clobetasol propionate, a synthetic fluorinated corticosteroid, for topical use. The corticosteroids constitute a class of primarily synthetic steroids used topically as anti-inflammatory and antipruritic agents. Clobetasol propionate is 21-chloro-9-fluoro-11β, 17-dihydroxy-16β -methylpregna-1,4-diene-3,20-dione 17-propionate, with the empirical formula C25H32CIFO5, and a molecular weight of 466.97 (CAS Registry Number 25122-46-7).

The following is the chemical structure:

Clobetasol propionate is a white to almost white crystalline powder that is practically insoluble in water. Each gram of CLOBEX® (clobetasol propionate) Spray, 0.05% contains 0.5 mg of clobetasol propionate, in a vehicle base composed of alcohol, isopropyl myristate, sodium lauryl sulfate, and undecylenic acid.

CLINICAL PHARMACOLOGY

Like other topical corticosteroids CLOBEX® (clobetasol propionate) Spray, 0.05% has anti-inflammatory, antipruritic, and vasoconstrictive properties. The mechanism of the anti-inflammatory activity of the topical steroids in general is unclear. However, corticosteroids are thought to act by induction of phospholipase A2 inhibitory proteins, collectively called lipocortins. It is postulated that these proteins control the biosynthesis of potent mediators of inflammation such as prostaglandins and leukotrienes by inhibiting the release of their common precursor, arachidonic acid. Arachidonic acid is released from membrane phospholipids by phospholipase A2.

Pharmacokinetics: The extent of percutaneous absorption of topical corticosteroids is determined by many factors, including the vehicle, the integrity of the epidermal barrier and occlusion. Topical corticosteroids can be absorbed from normal intact skin. Inflammation and other disease processes in the skin may increase percutaneous absorption.

There are no human data regarding the distribution of corticosteroids to body organs following topical application. Nevertheless, once absorbed through the skin, topical corticosteroids are handled through metabolic pathways similar to systemically administered corticosteroids. They are metabolized, primarily in the liver, and are then excreted by the kidneys. In addition, some corticosteroids and their metabolites are also excreted in the bile.

CLOBEX® (clobetasol propionate) Spray, 0.05% is in the super-high range of potency as compared with other topical corticosteroids in a vasoconstrictor study conducted in healthy subjects. However, similar blanching scores do not necessarily imply therapeutic equivalence.

The effect of CLOBEX® (clobetasol propionate) Spray, 0.05% on hypothalamic-pituitary-adrenal (HPA) axis function was investigated in adults in two studies. In the first study, patients with plaque psoriasis covering at least 20% of their body applied CLOBEX® (clobetasol propionate) Spray, 0.05% twice daily for up to 4 weeks. Fifteen percent (2 out of 13) of patients displayed adrenal suppression after 4 weeks of use based on the Cosyntropin Stimulation Test. The laboratory suppression was transient; all subjects returned to normal after cessation of drug use. In the second study, patients with plaque psoriasis covering at least 20% of their body applied CLOBEX® (clobetasol propionate) Spray, 0.05% twice daily for either 2 or 4 weeks. Nineteen percent (4 out of 21) of patients treated for 2 weeks and 20% (3 out of 15) of patients treated for 4 weeks displayed adrenal suppression at the end of treatment based on the Cosyntropin Stimulation Test. The laboratory suppression was transient; all subjects returned to normal after cessation of drug use. In these studies, HPA axis suppression was defined as serum cortisol level ≤18 μg/dL 30-min post cosyntropin (ACTH1-24) stimulation (See PRECAUTIONS).

CLINICAL STUDIES

The efficacy of CLOBEX® (clobetasol propionate) Spray, 0.05% in psoriasis has been demonstrated in two randomized, vehicle controlled clinical trials, which were identical in design. The studies were conducted in patients aged 18 years and older with moderate to severe plaque psoriasis. Patients were treated twice daily for up to 4 weeks with either CLOBEX® (clobetasol propionate) Spray, 0.05% or vehicle spray.

Patients were evaluated on their Overall Disease Severity, a 5-point scale based on scaling, erythema, and plaque elevation that classified subjects as clear, almost clear, mild, moderate, or severe/very severe. Only patients classified as moderate or severe/very severe at baseline were enrolled in the studies. The median percent body surface area (BSA) at baseline was 6% for the two studies. The numbers of patients scored as clear or almost clear at Weeks 2 and 4 are presented in Table 1.

Table 1-Number of Patients Clear or Almost Clear on the Overall Disease Severity Scale at Weeks 2 and 4
 |  | Study 1 |  | Study 2
 |  | CLOBEX® | Vehicle | CLOBEX® | Vehicle
 |  | N=60 | N=60 | N=60 | N=60
Week 2 | Clear | 1 (2%) | 0 (0%) | 0 (0%) | 0 (0%)
 | Almost Clear | 32 (53%) | 1 (2%) | 28 (47%) | 0 (0%)
Week 4 | Clear | 15 (25%) | 0 (0%) | 18 (30%) | 0 (0%)
 | Almost Clear | 32 (53%) | 2 (3%) | 31 (52%) | 1 (2%)

INDICATIONS AND USAGE

CLOBEX® (clobetasol propionate) Spray, 0.05% is a super-high potent topical corticosteroid formulation indicated for the treatment of moderate to severe plaque psoriasis affecting up to 20% body surface area (BSA) in patients 18 years of age or older (see PRECAUTIONS). Treatment should be limited to 4 consecutive weeks. The total dosage should not exceed 50 g (59 mL or 2 fl. oz.) per week.

Before prescribing for more than 2 weeks, any additional benefits of extending treatment to 4 weeks should be weighed against the risk of HPA axis suppression.

Patients should be instructed to use CLOBEX® (clobetasol propionate) Spray, 0.05% for the minimum amount of time necessary to achieve the desired results (see PRECAUTIONS).

Use in patients under 18 years of age is not recommended because safety has not been established and because numerically high rates of HPA axis suppression were seen with other clobetasol propionate topical formulations (see PRECAUTIONS: Pediatric Use).

CONTRAINDICATIONS

CLOBEX® (clobetasol propionate) Spray, 0.05% is contraindicated in patients who are hypersensitive to clobetasol propionate, to other corticosteroids, or to any ingredient in this preparation.

PRECAUTIONS

General

Clobetasol propionate is a highly potent topical corticosteroid that has been shown to suppress the HPA axis at the lowest doses tested.

In studies evaluating the potential for hypothalamic-pituitary-adrenal (HPA) axis suppression, using the Cosyntropin Stimulation Test, CLOBEX® (clobetasol propionate) Spray, 0.05% demonstrated rates of suppression that were comparable after 2 and 4 weeks of twice-daily use (19% and 15-20%, respectively), in adult patients with moderate to severe plaque psoriasis (≥ 20%BSA). In these studies, HPA axis suppression was defined as serum cortisol level ≤18 μg/dL 30-min post cosyntropin stimulation (See CLINICAL PHARMACOLOGY).

Patients with acute illness or injury may have increased morbidity and mortality with intermittent HPA axis suppression. Patients should be instructed to use CLOBEX® (clobetasol propionate) Spray, 0.05% for the minimum amount of time necessary to achieve the desired results (See INDICATIONS AND USAGE).

Systemic absorption of topical corticosteroids has caused reversible adrenal suppression with the potential for glucocorticosteroid insufficiency after withdrawal of treatment. Manifestations of Cushing’s syndrome, hyperglycemia, and glucosuria can also be produced in some patients by systemic absorption of topical corticosteroids while on treatment.

HPA axis suppression has not been evaluated in psoriasis patients treated with CLOBEX® (clobetasol propionate) Spray, 0.05% who are less than 18 years old. Pediatric patients may be more susceptible to systemic toxicity from equivalent doses due to their larger skin surface to body mass ratios (see PRECAUTIONS: Pediatric Use). The potential increase in systemic exposure does not correlate with any proven benefit, but may lead to an increased potential for hypothalamic-pituitary-adrenal (HPA) axis suppression.

Conditions which increase systemic absorption include the application of the more potent steroids, use over large surface areas, prolonged use, and the addition of occlusive dressings. Therefore, patients applying a topical steroid to a large surface area or to areas under occlusion should be evaluated periodically for evidence of adrenal suppression (see laboratory tests below). If adrenal suppression is noted, an attempt should be made to withdraw the drug, to reduce the frequency of application, or to substitute a less potent steroid. Recovery of HPA axis function is generally prompt upon discontinuation of topical corticosteroids. Infrequently, signs and symptoms of glucocorticosteroid insufficiency may occur requiring supplemental systemic corticosteroids. For information on systemic supplementation, see prescribing information for those products.

If irritation develops, CLOBEX® (clobetasol propionate) Spray, 0.05% should be discontinued and appropriate therapy instituted. Allergic contact dermatitis with corticosteroids is usually diagnosed by observing a failure to heal rather than noting a clinical exacerbation, as with most topical products not containing corticosteroids.

In the presence of dermatological infections, the use of an appropriate antifungal or antibacterial agent should be instituted. If a favorable response does not occur promptly, use of CLOBEX® (clobetasol propionate) Spray, 0.05% should be discontinued until the infection has been adequately controlled.

CLOBEX® (clobetasol propionate) Spray, 0.05% should not be used in the treatment of rosacea or perioral dermatitis, and should not be used on the face, groin, or axillae.

Information for Patients

Patients using topical corticosteroids should receive the following information and instructions:

- This medication is to be used as directed by the physician and should not be used longer than the prescribed time period.
- This medication should not be used for any disorder other than that for which it was prescribed.
- The treated skin area should not be bandaged, otherwise covered, or wrapped so as to be occlusive unless directed by the physician.
- Patients should wash their hands after applying the medication.
- Patients should report any signs of local or systemic adverse reactions to the physician.
- Patients should inform their physicians that they are using CLOBEX® (clobetasol propionate) Spray, 0.05% if surgery is contemplated.
- This medication is for external use only. It should not be used on the face, underarms, or groin area. Also avoid contact with the eyes and lips.
- As with other corticosteroids, therapy should be discontinued when control is achieved. If no improvement is seen within 2 weeks, contact the physician.
- Do not exceed 30 sprays per application or 60 sprays per day.
- Patients should not use more than 50 g (59 mL or 2 fl.oz.) per week of CLOBEX® (clobetasol propionate) Spray, 0.05%.

Instructions to the Pharmacist:

1. Remove the spray pump from the wrapper
2. Remove and discard the cap from the bottle
3. Keeping the bottle vertical, insert the spray pump into the bottle and turn clockwise until well-fastened
4. Dispense the bottle with the spray pump inserted

Laboratory Tests

The cosyntropin stimulation test may be helpful in evaluating patients for HPA axis suppression.

Carcinogenesis, Mutagenesis, Impairment of Fertility

Long-term animal studies have not been performed to evaluate the carcinogenic potential of clobetasol propionate.

Clobetasol propionate was negative in the in vitro mammalian chromosomal aberration test and in the in vivo mammalian erythrocyte micronucleus test.

The effect of subcutaneously administered clobetasol propionate on fertility and general reproductive toxicity was studied in rats at doses of 0, 12.5, 25, and 50 μg/kg/day. Males were treated beginning 70 days before mating and females beginning 15 days before mating through day 7 of gestation. A dosage level of less than 12.5 μg/kg/day clobetasol propionate was considered to be the no-observed-effect-level (NOEL) for paternal and maternal general toxicity based on decreased weight gain and for male reproductive toxicity based on increased weights of the seminal vesicles with fluid. The female reproductive NOEL was 12.5 μg/kg/day (ratio of animal dose to proposed human dose of 0.03 on a mg/m^2/day basis) based on reduction in the numbers of estrous cycles during the pre-cohabitation period and an increase in the number of nonviable embryos at higher doses.

Pregnancy Teratogenic Effects

Pregnancy Category C.

Corticosteroids have been shown to be teratogenic in laboratory animals when administered systemically at relatively low dosage levels. Some corticosteroids have been shown to be teratogenic after dermal application to laboratory animals.

Clobetasol propionate is absorbed percutaneously, and when administered subcutaneously it was a significant teratogen in both the rabbit and the mouse. Clobetasol propionate has greater teratogenic potential than steroids that are less potent.

The effect of clobetasol propionate on pregnancy outcome and development of offspring was studied in the rat.

Clobetasol propionate was administered subcutaneously to female rats twice daily (0, 12.5, 25, and 50 μg/kg/day) from day 7 of presumed gestation through day 25 of lactation or day 24 presumed gestation for those rats that did not deliver a litter. The maternal NOEL for clobetasol propionate was less than 12.5 μg/kg/day due to reduced body weight gain and feed consumption during the gestation period. The reproductive NOEL in the dams was 25 μg/kg/day (ratio of animal dose to proposed human dose of 0.07 on a mg/m^2/day basis) based on prolonged delivery at a higher dose level. The no-observed-adverse-effect-level (NOAEL) for viability and growth in the offspring was 12.5 μg/kg/day (ratio of animal dose to proposed human dose of 0.03 on a mg/m^2/day basis) based on incidence of stillbirths, reductions in pup body weights on days 1 and 7 of lactation, increased pup mortality, increases in the incidence of umbilical hernia, and increases in the incidence of pups with cysts on the kidney at higher dose levels during the preweaning period. The weights of the epididymides and testes were significantly reduced at higher dosages. Despite these changes, there were no effects on the mating and fertility of the offspring.

There are no adequate and well-controlled studies of the teratogenic potential of clobetasol propionate in pregnant women. CLOBEX® (clobetasol propionate) Spray, 0.05% should be used during pregnancy only if the potential benefit justifies the potential risk to the fetus.

Nursing Mothers

Systemically administered corticosteroids appear in human milk and could suppress growth, interfere with endogenous corticosteroid production, or cause other untoward effects. It is not known whether topical administration of corticosteroids could result in sufficient systemic absorption to produce detectable quantities in breast milk. Because many drugs are excreted in human milk, caution should be exercised when CLOBEX® (clobetasol propionate) Spray, 0.05% is administered to a nursing woman.

Pediatric Use

Use in patients under 18 years of age is not recommended, because safety has not been established and because numerically high rates of HPA axis suppression were seen with other clobetasol propionate topical formulations. Safety and effectiveness in pediatric patients treated with CLOBEX® (clobetasol propionate) Spray, 0.05% have not been established (see PRECAUTIONS: General).

Because of higher ratio of skin surface area to body mass, pediatric patients are at a greater risk than adults of HPA axis suppression and Cushing’s syndrome when they are treated with topical corticosteroids. They are therefore also at greater risk of glucocorticosteroid insufficiency during and/or after withdrawal of treatment. Adverse effects including striae have been reported with inappropriate use of topical corticosteroids in infants and children.

HPA axis suppression, Cushing’s syndrome, linear growth retardation, delayed weight gain, and intracranial hypertension have been reported in children receiving topical corticosteroids. Manifestations of adrenal suppression in children include low plasma cortisol levels and absence of response to ACTH stimulation. Manifestations of intracranial hypertension include bulging fontanelles, headaches, and bilateral papilledema.

Geriatric Use

Clinical studies of CLOBEX® (clobetasol propionate) Spray, 0.05% did not include sufficient numbers of patients aged 65 and over to adequately determine whether they respond differently than younger patients. In the two Phase 3 studies, 21 of the 240 patients (9%) were over the age of 65. In general, dose selection for an elderly patient should be made with caution, usually starting at the low end of the dosing range, reflecting the greater frequency of decreased hepatic, renal or cardiac function, and of concomitant disease or other drug therapy.

ADVERSE REACTIONS

In controlled, clinical trials with CLOBEX® (clobetasol propionate) Spray, 0.05%, the most common adverse reaction was burning at the site of application [40% of subjects treated with CLOBEX® (clobetasol propionate) Spray, 0.05% and 47% of subjects treated with Spray Vehicle]. Other commonly reported adverse reactions for CLOBEX® (clobetasol propionate) Spray, 0.05% and Spray Vehicle, respectively, are noted in Table 2.

Table 2 - Commonly Occurring Adverse Events
 | Clobetasol Propionate | Vehicle Spray
Adverse Reaction | 0.05% Spray | (N=120)
 | (N=120)
System Organ Class
General disorders and administration site conditions | 50 (42%) | 56 (47%)
Application site atrophy | 0 (0%) | 1 (1%)
Application site burning | 48 (40%) | 56 (47%)
Application site dryness | 2 (2%) | 0 (0%)
Application site irritation | 1 (1%) | 0 (0%)
Application site pain | 1 (1%) | 2 (2%)
Application site pigmentation changes | 1 (1%) | 0 (0%)
Application site pruritus | 4 (3%) | 3 (3%)
Infections and infestations | 17 (14%) | 12 (10%)
Influenza | 0 (0%) | 2 (2%)
Nasopharyngitis | 6 (5%) | 3 (3%)
Pharyngitis streptococcal | 1 (1%) | 0 (0%)
Upper respiratory tract infection | 10 (8%) | 2 (2%)
Skin and subcutaneous tissue disorders | 4 (3%) | 2 (2%)
Eczema asteatotic | 2 (2%) | 0 (0%)

Other adverse events occurred at rates less than 1.0%. Most local adverse events were rated as mild to moderate and they are not affected by age, race or gender. The following additional local adverse reactions have been reported with topical corticosteroids. They may occur more frequently with the use of occlusive dressings and higher potency corticosteroids, including clobetasol propionate. These reactions are listed in an approximate decreasing order of occurrence: folliculitis, acneiform eruptions, hypopigmentation, perioral dermatitis, allergic contact dermatitis, secondary infection, striae and miliaria.

Systemic absorption of topical corticosteroids has produced hypothalamic-pituitary-adrenal (HPA) axis suppression manifestations of Cushing’s syndrome, hyperglycemia, and glucosuria in some patients.

OVERDOSAGE

Topically applied CLOBEX® (clobetasol propionate) Spray, 0.05% can be absorbed in sufficient amount to produce systemic effects. (See PRECAUTIONS).

DOSAGE AND ADMINISTRATION

CLOBEX® (clobetasol propionate) Spray, 0.05% should be sprayed directly onto the affected skin areas twice daily and rubbed in gently and completely. Do not exceed 30 sprays per application or 60 sprays per day. (See INDICATIONS AND USAGE).

CLOBEX® (clobetasol propionate) Spray, 0.05% contains a super-high potent topical corticosteroid; therefore treatment should be limited to 4 weeks. Treatment beyond 2 weeks should be limited to localized lesions of moderate to severe plaque psoriasis that have not sufficiently improved after the initial 2 weeks of treatment with CLOBEX® (clobetasol propionate) Spray, 0.05%.

The total dosage should not exceed 50 g (59 mL or 2 fluid ounces) per week because of the potential for the drug to suppress the hypothalamic-pituitary-adrenal (HPA) axis.

Therapy should be discontinued when control has been achieved. If no improvement is seen within 2 weeks, reassessment of diagnosis may be necessary.

Use in pediatric patients younger than 18 years is not recommended because of the potential for HPA axis suppression. (See PRECAUTIONS: Pediatric Use).

Unless directed by physician,CLOBEX® (clobetasol propionate) Spray, 0.05% should not be used with occlusive dressings.

HOW SUPPLIED

CLOBEX® (clobetasol propionate) Spray, 0.05% is supplied in a white HDPE bottle with a white polypropylene cap and white LDPE liner in the following size:

2 fl oz/59 mL NDC 54868-5510-0

Storage: Keep tightly closed. Store under controlled room temperature conditions 20°C - 25°C (68°F - 77°F) with excursions permitted between 15°C and 30°C (59°F and 86°F). Do not freeze, refrigerate or store above 30°C. Spray is flammable; keep away from heat or flame.

US Patent Nos: 5,972,920; 5,990,100 and foreign patents pending.

Marketed by:
GALDERMA LABORATORIES, L.P.
Fort Worth, Texas 76177 USA

Manufactured by:
CPL
Mississauga, Ontario, Canada L5N 6L6
Made in Canada.
GALDERMA is a registered trademark.
www.clobex.com
2004953-0409
Revised: April 2009

Relabeling of "Additional Barcode" label by:
Physicians Total Care, Inc.
Tulsa, OK 74146

PATIENT INFORMATION

CLOBEX® (clobetasol propionate) Spray, 0.05%
For External Use Only
Not for Ophthalmic (Eye) Use

Read the Patient Information that comes with CLOBEX® (KLO-bex) Spray before you start using it and each time you get a refill. There may be new information. This leaflet does not take the place of talking with your doctor about your medical condition or your treatment.

What is CLOBEX® Spray?

CLOBEX® Spray is a medicine called a topical (skin use only) corticosteroid. It is used for a short time to reduce the inflammation and itching of moderate to severe plaque psoriasis.

CLOBEX® Spray is a super-high potent (very strong) topical corticosteroid. It is very important that you use CLOBEX® Spray only as directed, in order to avoid serious side effects.

Who should not use CLOBEX® Spray?

Do not use CLOBEX® Spray if you are allergic to any of its ingredients, or to any other corticosteroid. The active ingredient is clobetasol propionate. See the end of this leaflet for the complete list of other ingredients in CLOBEX® Spray.

CLOBEX® Spray is not recommended for use on anyone younger than 18 years of age because the adrenal glands may shut down. (see section on “What are the possible side effects of CLOBEX® Spray?”). Children have smaller body sizes and have a higher chance of side effects.

What should I tell my doctor before using CLOBEX® Spray?

Tell your doctor:

- if you are pregnant, think you are pregnant or plan to be pregnant. Talk with your doctor before using CLOBEX® Spray or if you are already using CLOBEX® Spray, as it is not known if CLOBEX® Spray can harm your unborn child.
- if you are breastfeeding. It is not known if CLOBEX® Spray passes into your milk.
- if you think you have a skin infection. You may need another medicine to treat the skin infection before you use CLOBEX® Spray.

Tell your doctor about all the other medicines and skin products you use, including prescription and non-prescription medicines, cosmetics, vitamins, and herbal supplements. Some medicines can cause serious side effects if used while you are using CLOBEX® Spray.

How should I use CLOBEX® Spray?

- Use CLOBEX® Spray exactly as directed by your doctor. CLOBEX® Spray is for skin use only.
- Make sure your skin is clean and dry before applying CLOBEX® Spray.
- Apply CLOBEX® Spray twice a day, once in the morning and once at night, or as directed by your doctor. Use only enough to cover the affected skin areas and rub in gently and completely. Do not exceed 30 sprays per application or 60 sprays per day. Do not apply CLOBEX® Spray to your face, underarms, or groin and avoid contact with eyes and lips.
- Wash your hands after using CLOBEX® Spray.
- If you forget to apply CLOBEX® Spray at the scheduled time, use it as soon as you remember. Then go back to your regular schedule. If it is about time for your next dose, apply just that one dose, and continue with your normal application schedule. Do not try to make up for the missed dose. If you miss several doses, tell your doctor.
- Throw away unused CLOBEX® Spray.

What should I avoid while using CLOBEX® Spray?

Do not do the following while using CLOBEX® Spray.

- Do not get CLOBEX® Spray on your face or lips, or in or near your eyes because this might cause irritation. If you do, use a lot of water to rinse the CLOBEX® Spray off your face, lips, or out of your eyes. If your eyes keep stinging after rinsing them well with water, call your doctor right away.
- Do not apply CLOBEX® Spray to your groin or armpits.
- Do not bandage or cover your treated areas unless your doctor tells you to do so.
- Do not wear tight fitting clothes over your treated skin areas.
- Do not use CLOBEX® Spray any longer than 2 weeks (14 days) for moderate to severe psoriasis.
- Do not use CLOBEX® Spray any longer than an extra 2 weeks (4 consecutive weeks total).
- Do not use more than 50 grams (59 mL or 2 fluid ounces) of CLOBEX® Spray a week. CLOBEX® Spray is available in a 2 oz. and 4.25 oz bottle.

What are the possible side effects of CLOBEX® Spray?

CLOBEX® Spray can pass through your skin. Too much CLOBEX® Spray passing through your skin can shut down your adrenal glands. This usually happens if you use too much CLOBEX® Spray, or you use it for too long. If this happens, your adrenal glands may not start working immediately once you stop using CLOBEX® Spray.

Shutting down of the adrenal glands can cause nausea, vomiting, fever, low blood pressure, heart attack, and even death because your body cannot respond to stress or illness. Your doctor may do special blood and urine tests to check your adrenal gland function while you are using CLOBEX® Spray.

Other possible side effects with CLOBEX® Spray include mild to moderate burning, stinging, itching, redness, irritation, and dry skin. Also, thinning of the skin, widening of small blood vessels in the skin, and skin discomfort at the site of application may happen. Sometimes your condition will get worse with use of CLOBEX® Spray.

If you go to another doctor for illness, injury, or surgery, tell that doctor that you are using CLOBEX® Spray.

Tell your doctor if you:

- are going to have surgery
- get sick or don't feel right. Call your doctor right away.
- have irritation of the treated skin area that does not go away.
- have any unusual effects that you do not understand.
- have affected areas that do not seem to be getting better after 2 weeks of using CLOBEX® Spray.

These are not all the possible side effects of CLOBEX® Spray. For more information, ask your doctor or pharmacist.

General information about the safe and effective use of CLOBEX® Spray.

Medicines are sometimes prescribed for conditions that are not mentioned in patient information leaflets. Do not use CLOBEX® Spray for a condition for which it was not prescribed. Do not give CLOBEX® Spray to other people, even if they have the same symptoms you have. It may harm them. Keep CLOBEX® Spray and all medicines out of reach of children.

This leaflet summarizes the most important information about CLOBEX® Spray. If you would like more information, talk with your doctor. You can ask your pharmacist or doctor for information about CLOBEX® Spray that is written for health professionals.

What are the ingredients of CLOBEX® Spray?

Active Ingredient: clobetasol propionate

Inactive Ingredients: alcohol, isopropyl myristate, sodium lauryl sulfate, and undecylenic acid.

Rx Only

Marketed by:
GALDERMA LABORATORIES, L.P.
Fort Worth, Texas 76177 USA
Manufactured by:
CPL
Mississauga, Ontario, Canada L5N 6L6
Made in Canada.
GALDERMA is a registered trademark.
www.clobex.com
2004953-0409
Revised: April 2009

PRINCIPAL DISPLAY PANEL

Clobex®
(clobetasol propionate)

Spray

0.05%

2 FL OZ
(59 mL)

WARNING: FLAMMABLE. AVOID FIRE, FLAME OR SMOKING DURING AND IMMEDIATELY FOLLOWING APPLICATION.

For external use only. Not for eye use.

Usual dosage: Apply twice daily, once in the morning and once at night. Use only enough to cover the affected areas. Do not apply to the face, underarms, or groin and avoid contact with eyes and lips. See package insert for complete prescribing information.

Each gram contains: Active: clobetasol propionate (0.5 mg). Inactive: alcohol, isopropyl myristate, sodium lauryl sulfate, and undecylenic acid

Store at controlled room temperature 68° to 77°F (15° - 25°C), excursions permitted between 59° and 86°F (15° - 30°C). Protect from freezing. Keep out of reach of children.

US Patent Nos: 5,972,920; 5,990,100 and foreign patents pending.